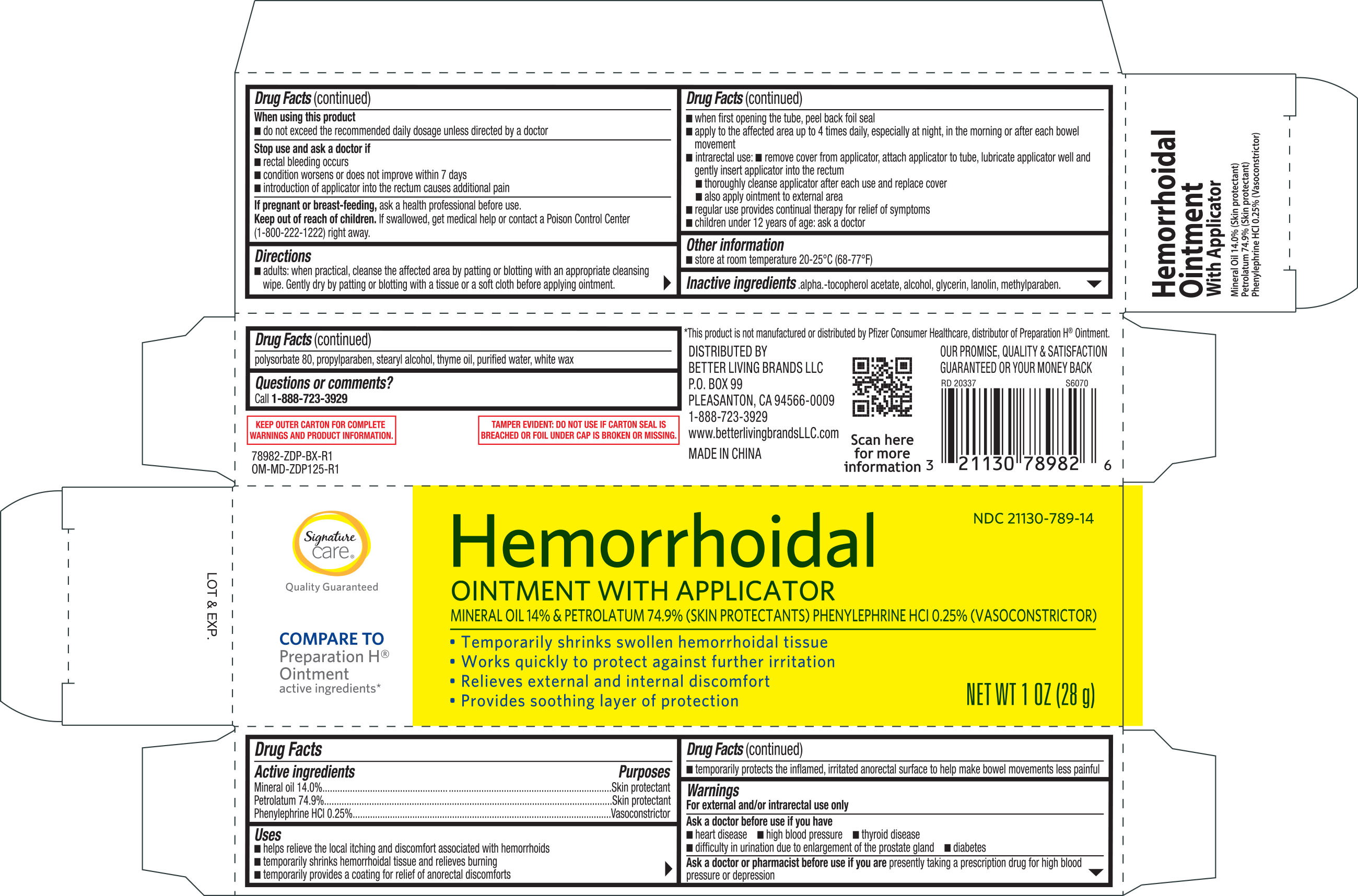 DRUG LABEL: Signature Care Hemorrhoidal
NDC: 21130-789 | Form: OINTMENT
Manufacturer: Better Living Brands, LLC
Category: otc | Type: HUMAN OTC DRUG LABEL
Date: 20260205

ACTIVE INGREDIENTS: PETROLATUM 749 mg/1 g; PHENYLEPHRINE HYDROCHLORIDE 2.5 mg/1 g; MINERAL OIL 140 mg/1 g
INACTIVE INGREDIENTS: GLYCERIN; LANOLIN; METHYLPARABEN; POLYSORBATE 80; PROPYLPARABEN; STEARYL ALCOHOL; THYME OIL; ALCOHOL; .ALPHA.-TOCOPHEROL ACETATE; WATER; WHITE WAX

Signature Care Hemorrhoidal Ointment 1 oz (with applicator) 78982 ZDP

Active ingredients Purpose

Mineral oil 14%..............................................Protectant

Petrolatum 74.9%..........................................Protectant

Phenylephrine HCI 0.25%..........................Vasconstrictor

Uses

- helps relieve the local itching and discomfort associated with hemorrhoids
- temporarily shrinks hemorrhoidal tissue and relieves burning
- temporarily provides a coating for relief of anorectal discomforts
- temporarily protects the inflamed, irritated anorectal surface to help bowel movements less painful

Warnings

For external and/or intrarectal use only

Ask a doctor before use if you have

- heart disease
- high blood pressure
- thyroid disease
- diabetes
- difficulty in urination due to enlargement of the prostate gland

Ask a doctor of pharmacist before use if you are presently taking a prescription drug for high blood pressure or depression.

When using this product do not exceed the recommended daily dosage unless directed by a doctor.

Stop use and ask a doctor if

- bleeding occurs
- condition worsens or does not improve within 7 days
- introduction of applicator into rectum causes additional pain

PREGNANCY OR BREAST FEEDING

If pregnant or breast-feeding, ask a health professional before use.

Keep out of reach of children. If swallowed, get medical help or contact a Poison Control right away.

Directions

- adults: when practical, cleanse the affected area by patting or blotting with an appropriate cleansing wipe. Gently dry by patting or blotting with a tissue or a soft cloth before applying ointment.
- when first opening the tube, puncture foil seal with top end of cap
- apply to the affected area up to 4 times daily, especially at night, in the morning or after each bowel movement
- interacetal use: remove cover from applicator, attach applicator to tube, lubricate applicator well and gently insert applicator into thoroughly cleanse applicator after each use and replace cover
- also apply ointment to external area
- regular use provides continual therapy for relief of symptoms
- children under 12 years of age: ask a doctor

Other information

- store at 20-25°C (68-77°F)
- Lot No. & Exp. Date: see box or see crimp of tube

Inactive ingredients

.alpha.-tocopherol acetate, alcohol, glycerin, lanolin, methylparaben, polysorbate 80, propylparaben, stearyl alcohol, thyme oil, purified water, white wax

DOSAGE AND ADMINISTRATION

Distributed by:

Better Living Brands LLC

P.O. Box 99

Pleasanton, CA 94566-0009

1-888-723-3929

www.betterlivingbrandsLLC.com

Made in China